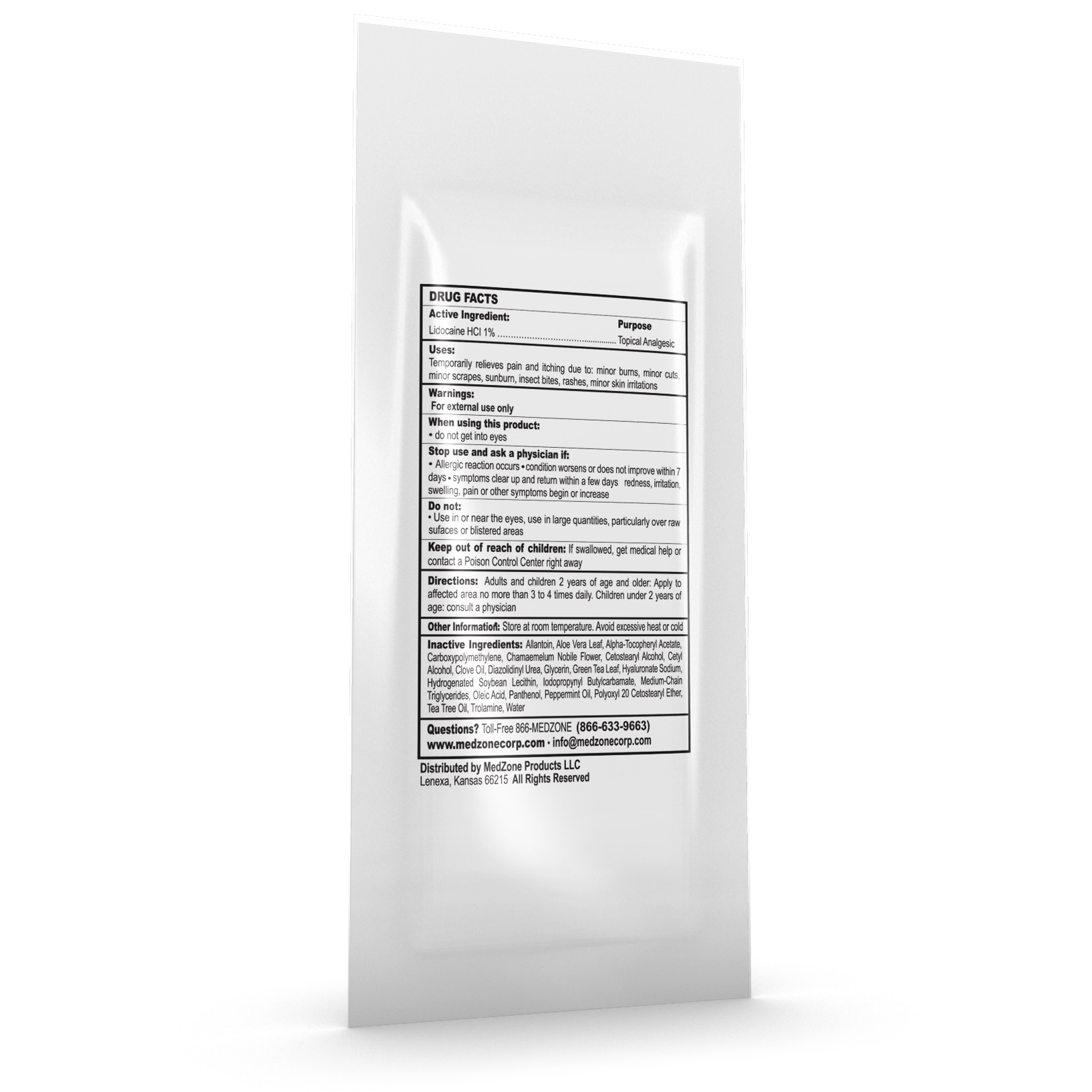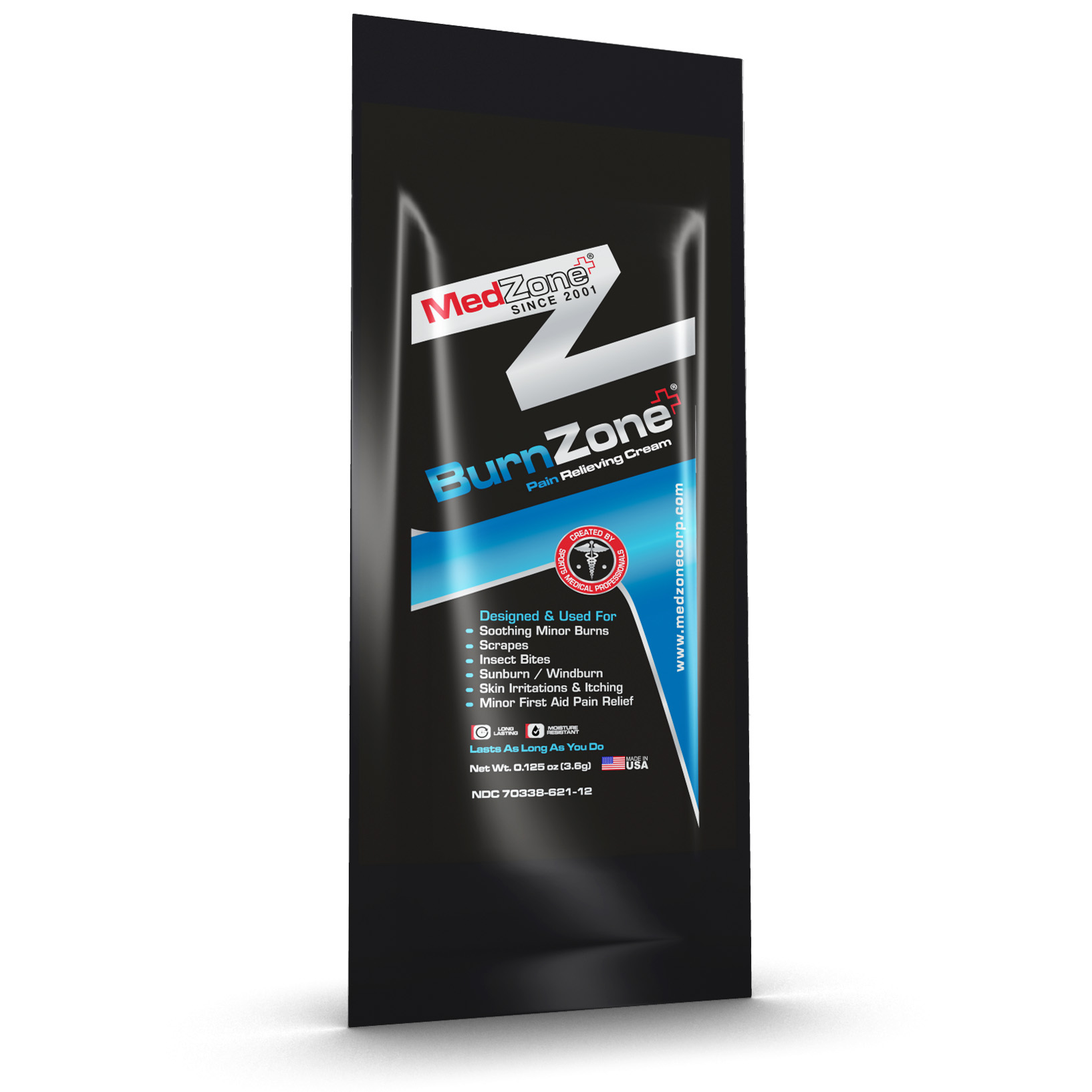 DRUG LABEL: BurnZone
NDC: 70338-621 | Form: CREAM
Manufacturer: MedZone Products LLC
Category: otc | Type: HUMAN OTC DRUG LABEL
Date: 20180212

ACTIVE INGREDIENTS: LIDOCAINE HYDROCHLORIDE 10 mg/1 g
INACTIVE INGREDIENTS: CARBOMER 934; CHAMAEMELUM NOBILE FLOWER; CETOSTEARYL ALCOHOL; CETYL ALCOHOL; IODOPROPYNYL BUTYLCARBAMATE; OLEIC ACID; PANTHENOL; TEA TREE OIL; CLOVE OIL; GLYCERIN; GREEN TEA LEAF; HYALURONATE SODIUM; HYDROGENATED SOYBEAN LECITHIN; MEDIUM-CHAIN TRIGLYCERIDES; PEPPERMINT OIL; POLYOXYL 20 CETOSTEARYL ETHER; ALOE VERA LEAF; ALPHA-TOCOPHEROL ACETATE; ALLANTOIN; DIAZOLIDINYL UREA; TROLAMINE; WATER

Active Ingredient

Lidocaine HCl 1%

Purpose

Topical Analgesic

Uses

Temporarily relieves pain and itching due to minor burns, minor cuts, minor scrapes, sunburn, insect bites, rashes, minor skin irritations.

Warnings

For external use only

When using this product

- do not get into eyes

Stop use and ask a physician if

- Allergic reaction occirs
- condition worsens or does not improve within 7 days
- symptoms clear up and return withina few days
- redness, irritation, swelling, pain or other symptoms begin or increase

Do not use

- in or near the eyes
- in large quantities, particularly over raw surfaces or blistered areas

Keep out of reach of children

If swallowed, get medical help or contact a Posion Control Center right away.

Directions

dults and children 2 years of age and over: Apply to affected area no more than 3 to 4 times daily. Children under 2 years of age: consult a physician.

Other Information

Store at room temperature. Avoid execssive heat or cold.

Inactive Ingredients

Allantoin, Aloe Vera Leaf, Alpha-Tocopheryl Acetate, Carboxypolymethylene, Chamaemelum Nobile Flower, Cetostearyl Alchol, Cetyl Alcohol, Clove Oil, Duazolidinyl Urea, Glycerin, Green Tea Leaf, Hyaluronate Sodium, Hydrogenated Soybean Lecithin, Iodopropynyl Butylcarbamate, Medium-Chain Triglycerides, Oleic Acid, Panthenol, Peppermint Oil, Polyoxyl 20 Cetostearyl Ether, Tea Tree Oil, Trolamine, Water

Questions?

Toll-free 866-MEDZONE (866-633-9663)

www.medzonecorp.com info@medzonecorp.com

HOW SUPPLIED

Distributed by MedZone Products LLC

Lenexa Kansas 66215 All Rights Reserved